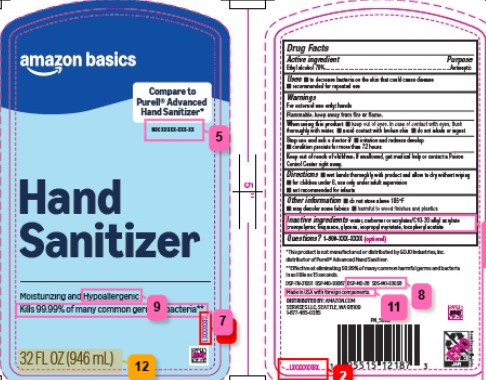 DRUG LABEL: Advanced
NDC: 72288-370 | Form: GEL
Manufacturer: Amazon.Com Services LLC
Category: otc | Type: HUMAN OTC DRUG LABEL
Date: 20260206

ACTIVE INGREDIENTS: ALCOHOL 70 mL/100 mL
INACTIVE INGREDIENTS: GLYCERYL CAPRYLATE/CAPRATE; GLYCERIN; ISOPROPYL MYRISTATE; .ALPHA.-TOCOPHEROL ACETATE; CARBOMER HOMOPOLYMER, UNSPECIFIED TYPE; CARBOMER COPOLYMER TYPE A (ALLYL PENTAERYTHRITOL CROSSLINKED); SULISOBENZONE; WATER

Basics 370.001/370AB/AE Rev1
Advanced Hand Sanitizer

Active ingredient

Ethyl alcohol 70%

Purpose

Antiseptic

Uses

- to decrease bacteria on the skin that could cause disease
- recommended for repeated use

Warnings

For external use only: hands

Flammable, keep away from fire or flame.

When using this product

- keep out of eyes. In case of contact with eyes, flush thoroughly with water.
- avoid contact with broken skin
- do not inhale or ingest

Stop use and ask a doctor if

- irritation and redness develop
- condition persists for more than 72 hours

Keep out of reach of children.

If swallowed, get medical help or contact a Poison Control Center right away.

Directions

- wet hands thoroughly with product and allow to dry without wiping
- for children under 6, use only under adult supervision
- not recommended for infants

Other information

- do not store above 105⁰ F
- may discolor some fabrics
- harmful to wood finishes and plastics

Inactive ingredients

water, glyceryl caprylate/caprate, glycerin, isopropyl myristate, tocopheryl acetate, carbomer or acrylates/C10-30 alkyl acrylate crosspolymer, fragrance, benzophenone-4

Disclaimer

*This product is not manufactured or distributed by GOJO Industries, Inc., distributor of PurellAdvanced Hand Sanitizer.

Claim

**Effective at eliminating 99.99% of many common harmful germs and bacteria in as little as 15 seconds.

Adverse Reaction

DSP-TN-21091 DSP-MO-20087

Made in USA with foreign components.

DISTRIBUTED BY: AMAZON.COM SERVICES LLC

Seattle, WA 98109

1-877-485-0385

principal display panel

amazon basics

Compare to Purell®Advanced Hand Sanitizer*

Hand Sanitizer

Moisturizing and Hypoallergenic

Kills 99.99% of many common germs and bacteria**

32 FL OZ (946 mL)